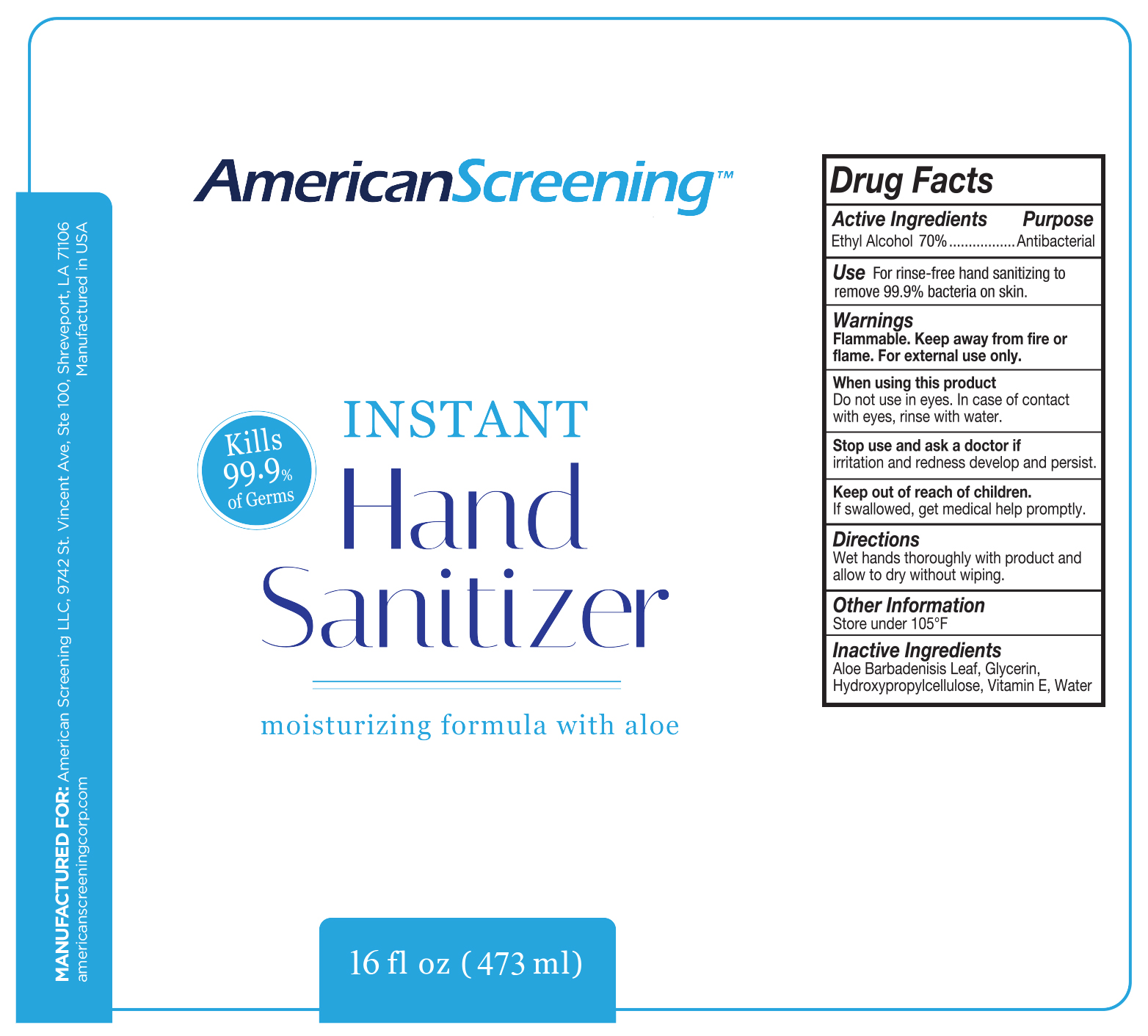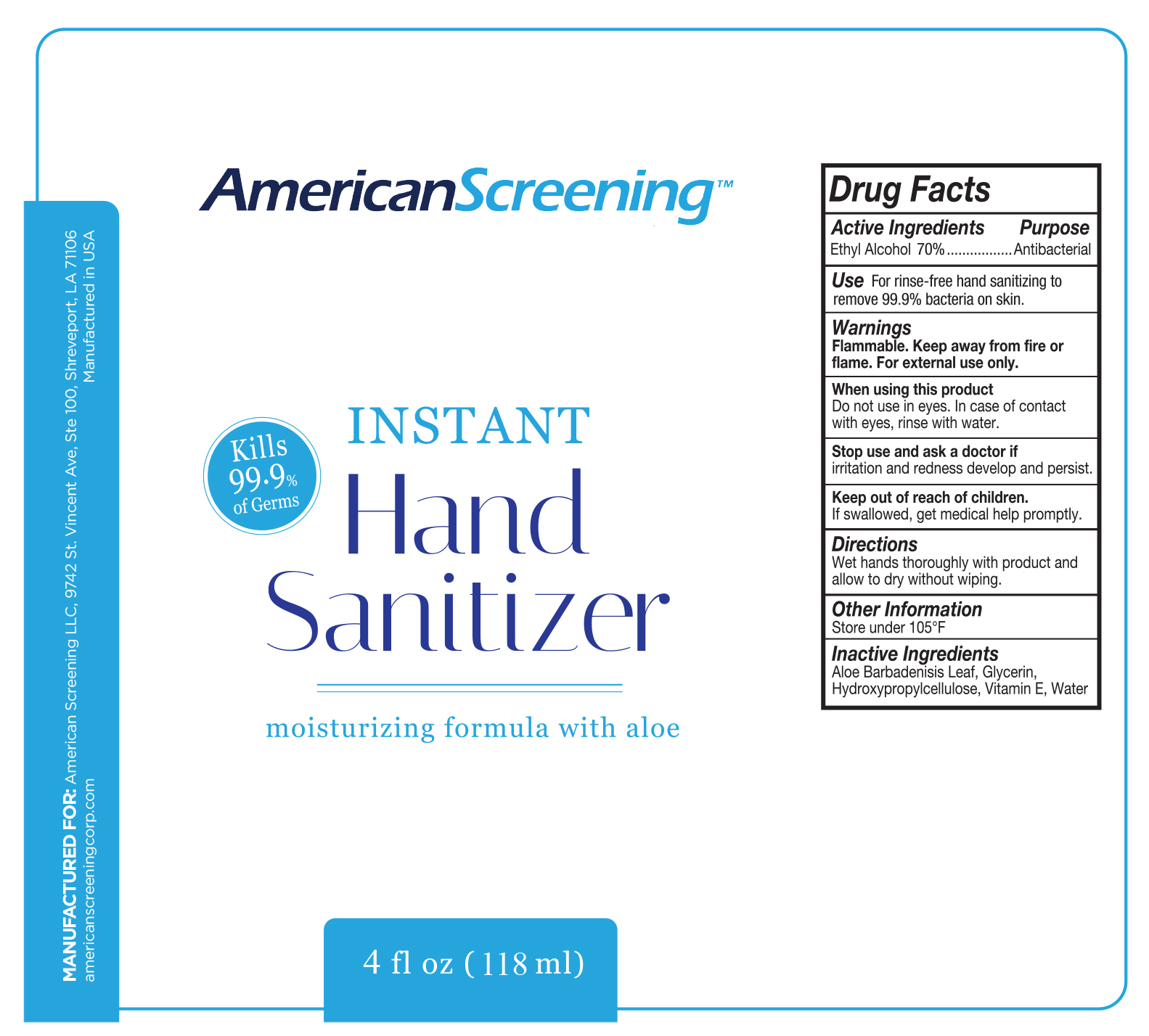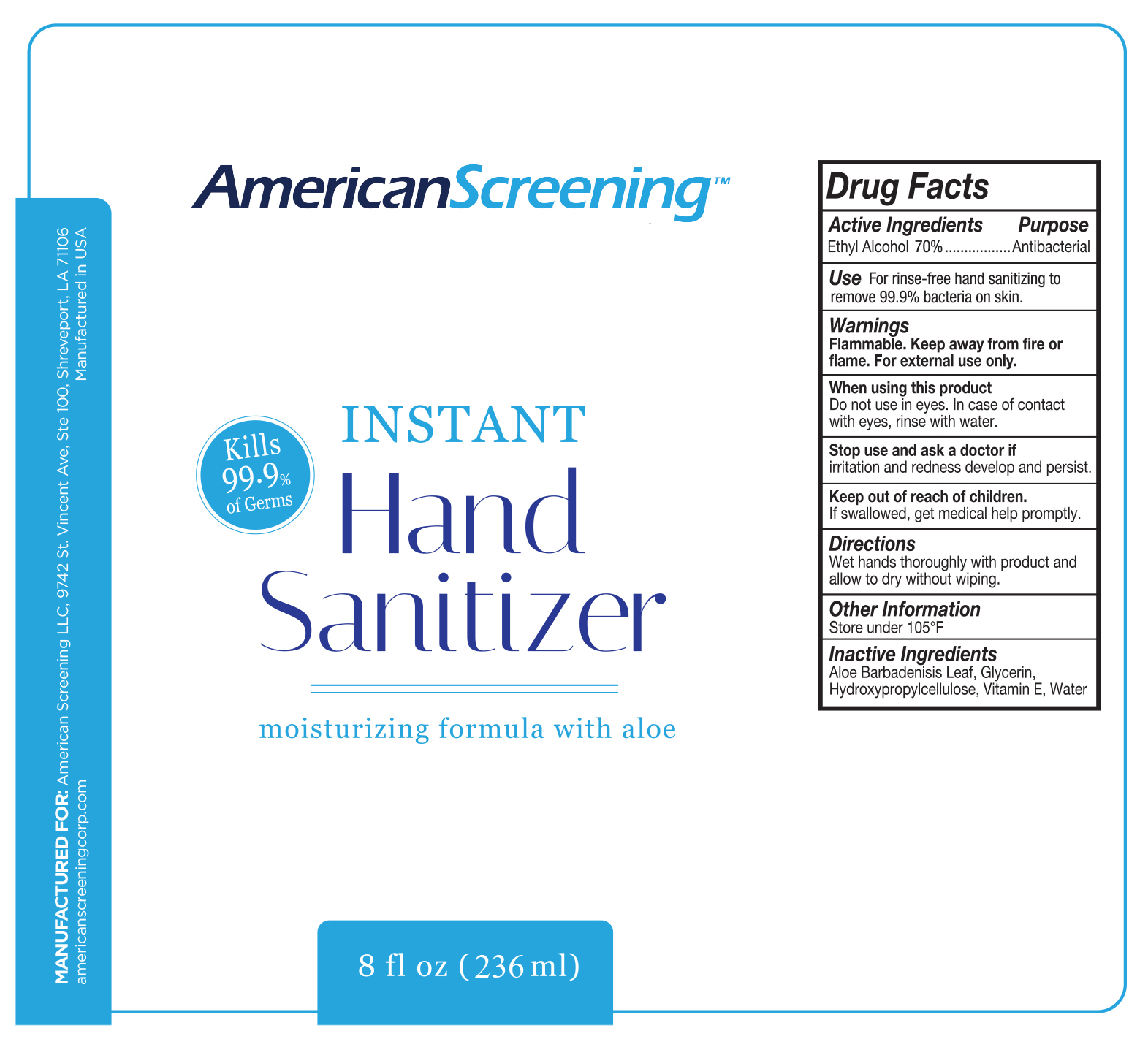 DRUG LABEL: Instant Hand Sanitizer
NDC: 73817-100 | Form: SOLUTION
Manufacturer: American Screening LLC
Category: otc | Type: HUMAN OTC DRUG LABEL
Date: 20211229

ACTIVE INGREDIENTS: ALCOHOL 70 L/100 L
INACTIVE INGREDIENTS: ALOE VERA LEAF; GLYCERIN; HYDROXYPROPYL CELLULOSE, UNSPECIFIED; .ALPHA.-TOCOPHEROL; WATER

Active Ingredients

Ethyl Alcohol 70%

Purpose

Antibacterial

Use

For rinse-free hand sanitizing to remove 99.9% bacteria on skin.

Warnings

Flammable. Keep away from fire or flame. For external use only.

When using this product

Do not use in eyes. In case of contact with eyes, rinse with water.

Stop use and ask a doctor if

irritation and redness develop and persist.

Keep out of reach of children.

If swallowed, get medical health promptly

Directions

Wet hands thoroughly with product and allow to dry without wiping.

Other Information

Store under 105°F

Inactive Ingredients

Aloe Barbadenisis Leaf, Glycerin, Hydroxypropylcellulose, Vitamin E, Water

PACKAGE LABEL

4 ounces (118 mL) - NDC 00000-000-00

8 ounces (236 mL) - NDC 00000-000-00

16 ounces (437 mL) - NDC 00000-000-00